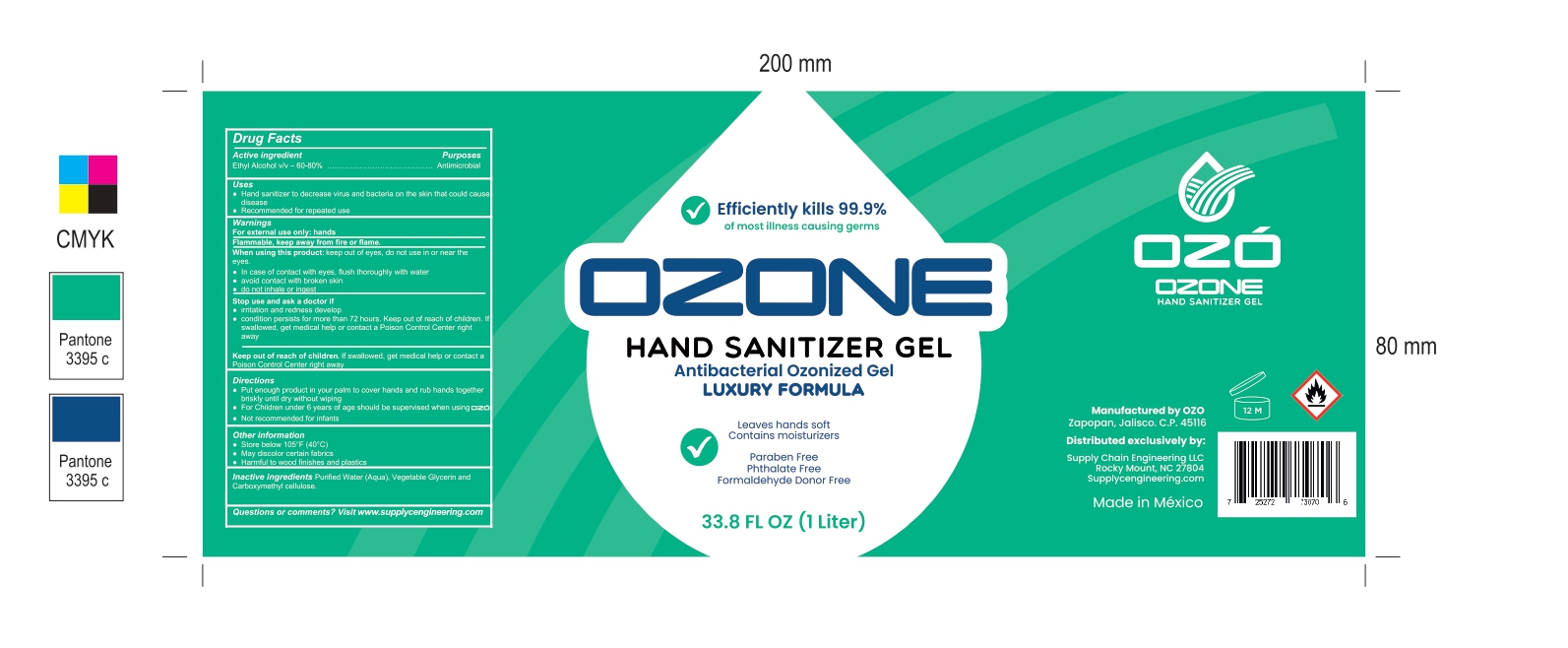 DRUG LABEL: HAND SANITIZER
NDC: 77210-0001 | Form: GEL
Manufacturer: EXPORTADORA IN & OUT S DE RL DE CV
Category: otc | Type: HUMAN OTC DRUG LABEL
Date: 20200505

ACTIVE INGREDIENTS: ALCOHOL 70 mL/100 mL
INACTIVE INGREDIENTS: WATER; CARBOXYMETHYLCELLULOSE 0.4 mL/100 mL; GLYCERIN 0.4 mL/100 mL

Active Ingredients

Alcohol 70% v/v. Porpuse: Antimicrobial

Purpose

Antimicrobial

uses

- Hand sanitizer to decrease virus and bacteria on the skin that could cause disease

-Recomended for repeated use

warnings

For external use only: hands

Flammable, keep away from fire or flame.

Stop use and ask a doctor if

-irritation and redness develop

-condition persist for more than 72 hours. Keep out of reach of childre. If swallowed, get medical help or contact a Poison Control Center right away

keep out of reach of children

If swallowed, get medical help or contact a Poison Control center right away

when using this product

keep out of eyes, do not use in or near the eyes.

In case of contact with eyes, flush thoroughly with water

avoid contact with broken skin

do not inhale or ingest

Directions

-Put enough product in your palm to cover hands and rub hands together briskly until dry without wiping

-For children under 6 years of age should be supervised when using OZO

-Not recommended for infants

Other information

-Store below 105 F (40 C)

-May discolor certain fabrics

-Harmful to wood finishes and plastics

Inactive ingredients

Purified water (Aqua), Vegetable Glycerin, and Carboxymethyl cellulose

Questions or comments?

Visit www.supplycengineering.com

directions

-Put enough product in your palm to cover hands and rub hands together briskly until dry without wiping

-For Children under 6 years of age should be supervised when using OZO

-Not recommended for infants

Warnings

For external use only: hands

Flammable, keep away from fire or flame

principal display

efficiently kills 99.9% of most illnes causing germs

OZONE

hand sanitizer gel

antibacterial ozonized gel

luxury formula

leaves hands soft

contain moisturizers

paraben free

phthalate free

formaldehyde donor free

33.8 FL OZ (1 Liter)